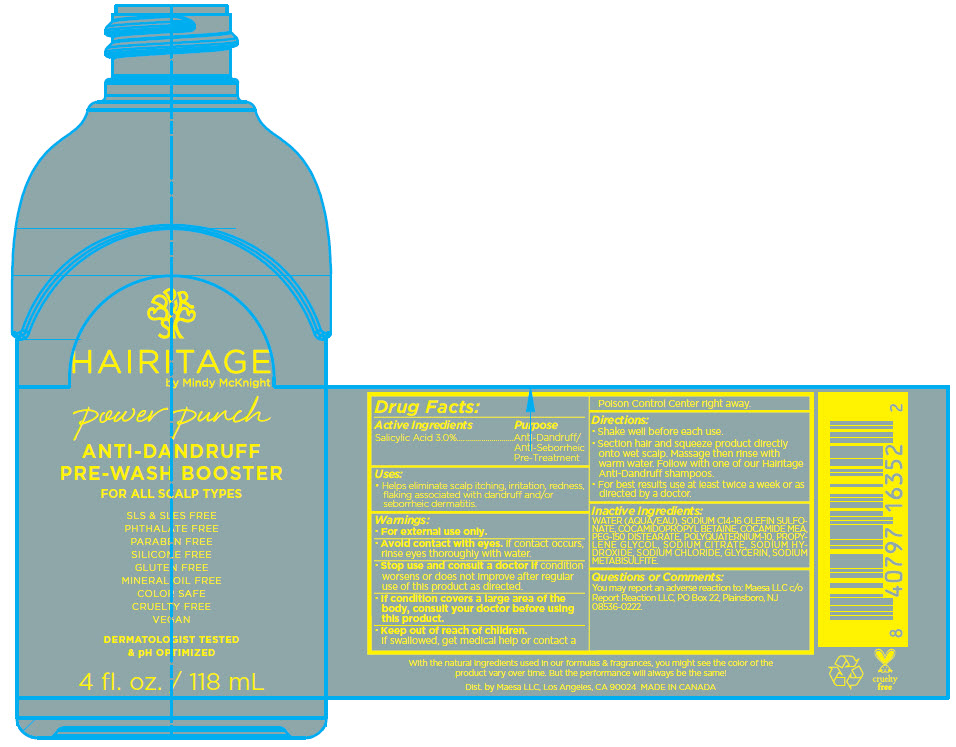 DRUG LABEL: Hairitage Power Punch Anti-Dandruff Pre-Wash Booster
NDC: 71899-067 | Form: LIQUID
Manufacturer: Maesa, LLC.
Category: otc | Type: HUMAN OTC DRUG LABEL
Date: 20241112

ACTIVE INGREDIENTS: Salicylic Acid 3 mg/118 mL
INACTIVE INGREDIENTS: Sodium C14-16 Olefin Sulfonate; Sodium Hydroxide; Cocamidopropyl Betaine; Sodium Chloride; Glycerin; Sodium Metabisulfite; COCO MONOETHANOLAMIDE; PEG-150 distearate; POLYQUATERNIUM-10 (400 MPA.S AT 2%); PROPYLENE GLYCOL; SODIUM CITRATE, UNSPECIFIED FORM; Water

Hairitage Power Punch Anti-Dandruff Pre-Wash Booster

Drug Facts:

Active Ingredients

Salicylic Acid 3.0%

Purpose

Anti-Dandruff/Anti-Seborrheic Pre-Treatment

Uses

- Helps eliminate scalp itching, irritation, redness, flaking associated with dandruff and/or seborrheic dermatitis.

Warnings

- For external use only.

- Avoid contact with eyes. If contact occurs, rinse eyes thoroughly with water.

- Stop use and consult a doctor if condition worsens or does not improve after regular use of this product as directed.

- If condition covers a large area of the body, consult your doctor before using this product.

- Keep out of reach of children. If swallowed, get medical help or contact a Poison Control Center right away.

Directions

- Shake well before each use.
- Section hair and squeeze product directly onto wet scalp. Massage then rinse with warm water. Follow with one of our Hairitage Anti-Dandruff shampoos.
- For best results use at least twice a week or as directed by a doctor.

Inactive Ingredients

WATER (AQUA/EAU), SODIUM C14-16 OLEFIN SULFONATE, COCAMIDOPROPYL BETAINE, COCAMIDE MEA, PEG-150 DISTEARATE, POLYQUATERNIUM-10, PROPYLENE GLYCOL, SODIUM CITRATE, SODIUM HYDROXIDE, SODIUM CHLORIDE, GLYCERIN, SODIUM METABISULFITE.

Questions or Comments

You may report an adverse reaction to: Maesa LLC c/o Report Reaction LLC, PO Box 22, Plainsboro, NJ 08536-0222.

Dist. by Maesa LLC, Los Angeles, CA 90024

PRINCIPAL DISPLAY PANEL - 118 mL Bottle Label

HAIRITAGE
by Mindy McKnight

power punch

ANTI-DANDRUFF
PRE-WASH BOOSTER

FOR ALL SCALP TYPES

SLS & SLES FREE
PHTHALATE FREE
PARABEN FREE
SILICONE FREE
GLUTEN FREE
MINERAL OIL FREE
COLOR SAFE
CRUELTY FREE
VEGAN

DERMATOLOGIST TESTED
& pH OPTIMIZED

4 fl. oz. / 118 mL